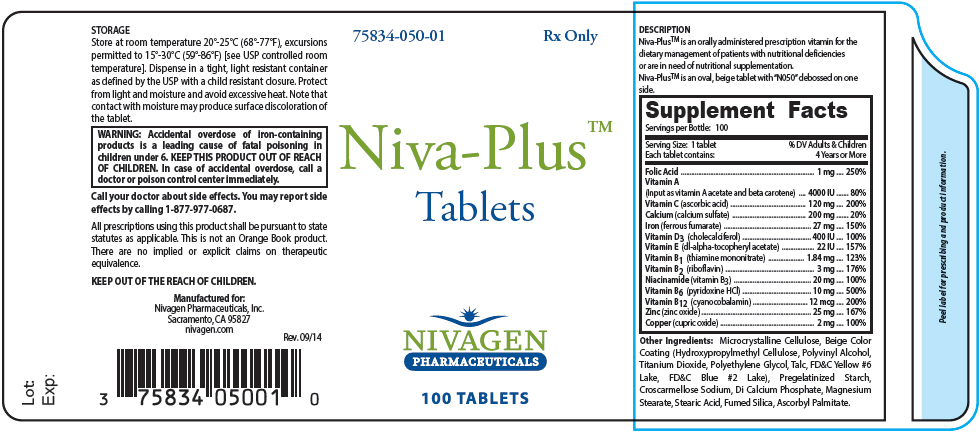 DRUG LABEL: Niva-Plus
NDC: 75834-050 | Form: TABLET, COATED
Manufacturer: Nivagen Pharmaceuticals, Inc.
Category: other | Type: DIETARY SUPPLEMENT
Date: 20150312

ACTIVE INGREDIENTS: FOLIC ACID 1 mg/1 1; VITAMIN A 4000 [iU]/1 1; ASCORBIC ACID 120 mg/1 1; CALCIUM SULFATE 200 mg/1 1; FERROUS FUMARATE 27 mg/1 1; CHOLECALCIFEROL 400 [iU]/1 1; .ALPHA.-TOCOPHEROL ACETATE, DL- 22 [iU]/1 1; THIAMINE MONONITRATE 1.84 mg/1 1; RIBOFLAVIN 3 mg/1 1; NIACINAMIDE 20 mg/1 1; PYRIDOXINE HYDROCHLORIDE 10 mg/1 1; CYANOCOBALAMIN 12 ug/1 1; ZINC OXIDE 25 mg/1 1; CUPRIC OXIDE 2 mg/1 1
INACTIVE INGREDIENTS: CELLULOSE, MICROCRYSTALLINE; HYPROMELLOSES; POLYVINYL ALCOHOL; TITANIUM DIOXIDE; POLYETHYLENE GLYCOLS; TALC; FD&C YELLOW NO. 6; ALUMINUM OXIDE; FD&C BLUE NO. 2; CROSCARMELLOSE SODIUM; CALCIUM PHOSPHATE, DIBASIC, ANHYDROUS; MAGNESIUM STEARATE; STEARIC ACID; SILICON DIOXIDE; ASCORBYL PALMITATE

Niva-Plus™
Tablets

HEALTH CLAIM

Rx Only

DESCRIPTION

Niva-Plus™ is an orally administered prescription vitamin for the dietary management of patients with nutritional deficiencies or are in need of nutritional supplementation. Niva-Plus™ is an oval, beige tablet with "N050" debossed on one side.

HEALTH CLAIM

Supplement Facts
Servings per Bottle: 100
Serving Size: 1 tablet Each tablet contains: | % DV Adults & Children 4 Years or More
Folic Acid | 1 mg | 250%
Vitamin A (Input as vitamin A acetate and beta carotene) | 4000 IU | 80%
Vitamin C (ascorbic acid) | 120 mg | 200%
Calcium (calcium sulfate) | 200 mg | 20%
Iron (ferrous fumarate) | 27 mg | 150%
Vitamin D3 (cholecalciferol) | 400 IU | 100%
Vitamin E (dl-alpha-tocopheryl acetate) | 22 IU | 157%
Vitamin B1 (thiamine mononitrate) | 1.84 mg | 123%
Vitamin B2 (riboflavin) | 3 mg | 176%
Niacinamide (vitamin B3) | 20 mg | 100%
Vitamin B6 (pyridoxine HCl) | 10 mg | 500%
Vitamin B12 (cyanocobalamin) | 12 mcg | 200%
Zinc (zinc oxide) | 25 mg | 167%
Copper (cupric oxide) | 2 mg | 100%

Other Ingredients: Microcrystalline Cellulose, Beige Color Coating (Hydroxypropylmethyl Cellulose, Polyvinyl Alcohol, Titanium Dioxide, Polyethylene Glycol, Talc, FD&C Yellow #6 Lake, FD&C Blue #2 Lake), Pregelatinized Starch, Croscarmellose Sodium, Di Calcium Phosphate, Magnesium Stearate, Stearic Acid, Fumed Silica, Ascorbyl Palmitate.

INDICATIONS AND USAGE

Niva-Plus™ is indicated for the supplemental requirements of patients with nutritional deficiencies or are in need of nutritional supplementation.

CONTRAINDICATIONS

This product is contraindicated in patients with known hypersensitivity to any of the ingredients.

WARNINGS

WARNING: Accidental overdose of iron-containing products is a leading cause of fatal poisoning in children under 6. KEEP THIS PRODUCT OUT OF REACH OF CHILDREN. In case of accidental overdose, call a doctor or poison control center immediately.

PRECAUTIONS

General

Folic acid, when prescribed as a single agent in doses above 0.1 mg daily, may obscure the detection of B12 deficiency (specifically, the administration of folic acid may reverse the hematological manifestations of B12 deficiency, including pernicious anemia, while not addressing the neurological manifestations). Reduced folates may be less likely than folic acid to mask vitamin B12 deficiency. Folate therapy alone is inadequate for the treatment of B12 deficiency.

PATIENT INFORMATION

Niva-Plus™ is a prescription vitamin for the use only under the direction and supervision of a licensed physician.

INTERACTIONS

Pyridoxine hydrochloride should not be given to patients receiving the drug levodopa, because the action of levodopa is antagonized by pyridoxine hydrochloride. However, pyridoxine hydrochloride may be used concurrently in patients receiving a preparation containing both carbidopa and levodopa.

Drugs which may interact with folate include:

- Antiepileptic drugs (AED): The AED class including, but not limited to, phenytoin, carbamazepine, primidone, valproic acid, phenobarbital and lamotrigine have been shown to impair folate absorption and increase the metabolism of circulating folate. Additionally, concurrent use of folic acid has been associated with enhanced phenytoin metabolism, lowering the levels of this AED in the blood and allowing breakthrough seizures to occur.
- Capecitabine: Folinic acid (5-formyltetrahydrofolate) may increase the toxicity of Capecitabine.
- Cholestyramine: Reduces folic acid absorption and reduces serum folate levels.
- Colestipol: Reduces folic acid absorption and reduces serum folate levels.
- Cycloserine: Reduces folic acid absorption and reduces serum folate levels.
- Dihydrofolate Reductase Inhibitors (DHFRI): DHFRIs block the conversion of folic acid to its active forms, and lower plasma and red blood cell folate levels. DHFRIs include aminopterin, methotrexate, pyrimethamine, triamterene, and trimethoprim.
- Fluoxetine: Fluoxetine exerts a noncompetitive inhibition of the 5-methyltetrahydrofolate active transport in the intestine.
- Isotretinoin: Reduced folate levels have occurred in some patients taking isotretinoin.
- Nonsteroidal Anti-inflammatory Drugs (NSAIDs): NSAIDs have been shown to inhibit some folate dependent enzymes in laboratory experiments. NSAIDs include ibuprofen, naproxen, indomethacin and sulindac.
- Oral Contraceptives: Serum folate levels may be depressed by oral contraceptive therapy.
- Methylprednisolone: Reduced serum folate levels have been noted after treatment with methylprednisolone.
- Pancreatic Enzymes: Reduced folate levels have occurred in some patients taking pancreatic extracts.
- Pentamidine: Reduced folate levels have been seen with prolonged intravenous pentamidine.
- Smoking and alcohol: Reduced serum folate levels have been noted.
- Sulfasalazine: Inhibits the absorption and metabolism of folic acid.
- Metformin treatment in patients with type 2 diabetes decreases serum folate.
- Warfarin can produce significant impairment in folate status after a 6 - month therapy.

ADVERSE REACTIONS

Allergic sensitization has been reported following both oral and parenteral administration of folic acid, as well as possibly the use of other forms of folates - including reduced folates. Paresthesia, somnolence, nausea and headaches have been reported with pyridoxine hydrochloride. Mild transient diarrhea, polycythemia vera, itching, transitory exanthema and the feeling of swelling of the entire body have been associated with cyanocobalamin.

Ferrous Fumarate

Gastrointestinal disturbances (anorexia, nausea, diarrhea, constipation) occur occasionally, but are usually mild and subside with continuation of therapy and physician encouragement. Although, the absorption of iron is best when taken between meals, occasional gastrointestinal disturbances may be controlled giving Niva-Plus™ shortly after meals.

DOSAGE AND ADMINISTRATION

Before, during and after pregnancy, one tablet daily, or as prescribed by a physician.

HOW SUPPLIED

Niva-Plus™ is supplied as:

Bottles of 100 tablets: 75834-050-01

KEEP OUT OF REACH OF CHILDREN

HEALTH CLAIM

Rx Only

Manufactured for:
Nivagen Pharmaceuticals, Inc., Sacramento, CA 95827
nivagen.com

Rev. 09/14

PRINCIPAL DISPLAY PANEL - 100 Tablet Bottle Label

75834-050-01
Rx Only

Niva-Plus™
Tablets

NIVAGEN
PHARMACEUTICALS

100 TABLETS